DRUG LABEL: Okcheonwon
NDC: 72850-0008 | Form: PILL
Manufacturer: Chunwoo Pharmaceutical Co., Ltd.
Category: homeopathic | Type: HUMAN OTC DRUG LABEL
Date: 20220131

ACTIVE INGREDIENTS: LICORICE 13.9 mg/10 g; TRICHOSANTHES KIRILOWII ROOT 20.8 mg/10 g; PUERARIA MONTANA VAR. LOBATA ROOT 20.8 mg/10 g; LIRIOPE MUSCARI ROOT 13.9 mg/10 g; PRUNUS MUME FRUIT 13.9 mg/10 g; ASTRAGALUS MONGHOLICUS ROOT 13.9 mg/10 g; ASIAN GINSENG 13.9 mg/10 g; OPHIOPOGON JAPONICUS ROOT 13.9 mg/10 g
INACTIVE INGREDIENTS: LACTOSE MONOHYDRATE

Okcheonwon

Active ingredients

Trichosanthes Kirilowii Root }

Pueraria Lobata Root }

Liriope Muscari Root }

Ophiopogon japonicus Root } ------------------------------------------------ Diabetes

Prunus Mume Fruit }

Astragalus Mongholicus Root }

Asian Ginseng }

Licorice }

Purpose

Diabetes

Directions

For adults, take 1 case (15 pills)l a day, before or between meals

Inactive ingredients

Corn Starch, Animal originated ingredients: Lactose Hydrate/Cow Milk

Keep out of reach of children. If swallowed, get medical help or contact a Poison Control Center (1-800-222-1222) right away.

Warnings

Do not use if you have

- galactose intolerance
- lapp lactase deficiency
- glucose-galactose malabsorption (this medicine contains lactose)

Ask a doctor before use if you are

- a hypertensive
- a heart or kidney patient
- an edema patient
- a patient who is being treated by a doctor or taking other medications.
- an elderly person (in general, elderly people should take with care, such as reducing their dosage, as their physiological function has deteriorated.)
- a child (the safety of children's use is not established. (Less experience in use))

Stop use and ask a doctor, pharmacist or health professionals and bring this if you have following symptoms after use:

- Pseudohyperaldosteronism: Reduced urine volume, swollen face, swollen hands and feet, heavy eyelids, firm hands, increased blood pressure, headache, and etc. (Mediciness with a maximum daily dose of 1g or more may develop hypoglycemia, blood pressure rise, low sodium body fluid, edema, weight gain, and etc. caused by pseydohyperaldosteronism if taken continuously for a long time. Therefore, make sufficient observations (measurement of serum potassium levels) and stop taking if there is any abnormality.)
- Myopathy: Myopathy (muscle disease) may occur as a result of hypokalemia, so take sufficient observation and stop taking if you find any abnormalities such as feeling helplessness, limb cramps, paralysis, and etc.
- Skin trouble: a rash, itch, bloodshot, and etc.
- Digestive system disorder: anorexia, stomach discomfort, nausea, vomiting, and etc.
- Liver disorder: jaundice, fatigue, and etc.
- Interstitial lung disease: difficult to breathe, fever, and etc. accompanied by a cough.
- Urinary system disorder: dysuria
- The autonomic system disorder: insomnia, excessive sweating, fast pulse, frequent urination, palpitations, feeling helplessness, excitement, and etc.

- If there is no improvement in symptoms after taking it for one month

Other Warnings

- do not take more than directed
- when taken with potassium-containing agents, licorice-containing agents, glycirizinic acid or other related agents, loop diuretics (furosemide, ethacrynic acid), or thiazide diuretics (trichlormethiazide) and myopathy, it is likely to appear due to gastric aldosterone (pseudohyperaldosteronism) or hypokalemia
- if taken with other herbal medicines, be careful of overlapping of the crude medicines.
- in principle, you should not to take it continuously for a long time, but if it is necessary, consult with a doctor, herb doctor, dentist, pharmacist, or other health care professionals.
- it is easy to experience symptoms such as insomnia, hyperhidrosis, rapid pulse, frequent urination, palpitations, general fatigue, and mental excitement when use with Ephedra Sinica Stem or ephedrine-containing agents, MAO inhibitors, thyroid agents (thyroxine, liothyronine), catecholamine (epinephrine, isoprenaline) and xanthine agents (theophylline, diprophylline) so take it carefully, such as reducing the dose.

Uses

Thirst from diabetes